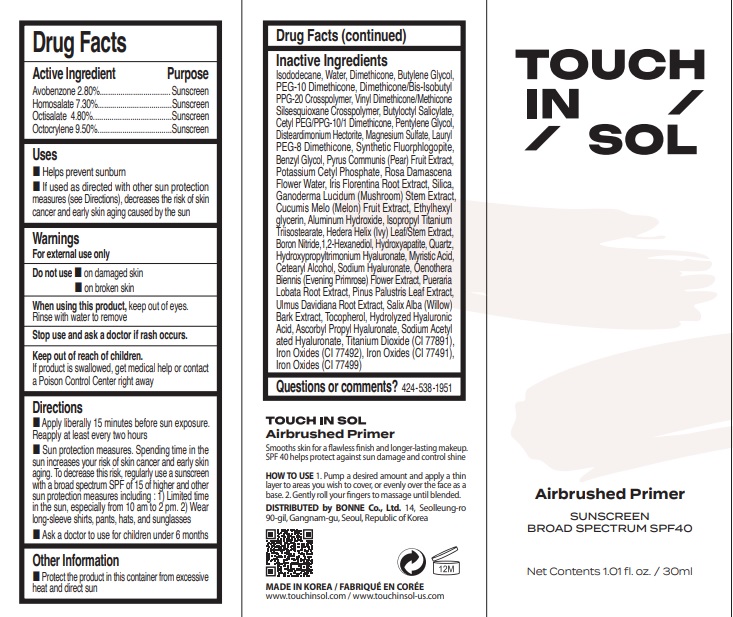 DRUG LABEL: Touch in SOL No Poreblem Airbrushed Primer
NDC: 69997-999 | Form: LOTION
Manufacturer: BONNE Co., Ltd
Category: otc | Type: HUMAN OTC DRUG LABEL
Date: 20260129

ACTIVE INGREDIENTS: OCTOCRYLENE 2.85 g/30 g; OCTISALATE 1.44 g/30 g; AVOBENZONE 0.84 g/30 g; HOMOSALATE 2.19 g/30 g
INACTIVE INGREDIENTS: HYALURONIC ACID; OENOTHERA BIENNIS FLOWER; CETEARYL ALCOHOL; BUTYLOCTYL SALICYLATE; PENTYLENE GLYCOL; SILICA; ISOPROPYL TITANIUM TRIISOSTEARATE; HEDERA HELIX LEAF; ROSA DAMASCENA FLOWER OIL; DIMETHICONE; DIMETHICONE/BIS-ISOBUTYL PPG-20 CROSSPOLYMER; ALUMINUM HYDROXIDE; CI 77491; SODIUM HYALURONATE; PUERARIA MONTANA VAR. LOBATA ROOT; IRIS GERMANICA VAR. FLORENTINA ROOT; LAURYL PEG-8 DIMETHICONE (300 CPS); CI 77499; PEG-10 DIMETHICONE (600 CST); CETYL PEG/PPG-10/1 DIMETHICONE (HLB 2); BENZYL GLYCOL; PYRUS COMMUNIS (PEAR) FRUIT; SODIUM ACETYLATED HYALURONATE; POTASSIUM CETYL PHOSPHATE; TOCOPHEROL; BORON NITRIDE; 1,2-HEXANEDIOL; HYDROXYAPATITE; MAGNESIUM POTASSIUM ALUMINOSILICATE FLUORIDE; ETHYLHEXYLGLYCERIN; ISODODECANE; BUTYLENE GLYCOL; CI 77492; GANODERMA LUCIDUM STEM; MUSKMELON; VINYL DIMETHICONE/METHICONE SILSESQUIOXANE CROSSPOLYMER; SALIX ALBA BARK; WATER; MYRISTIC ACID; PINUS PALUSTRIS LEAF; TITANIUM DIOXIDE; DISTEARDIMONIUM HECTORITE; ULMUS DAVIDIANA ROOT; MAGNESIUM SULFATE

WHEN USING

■ Helps prevent sunburn

■ if used as directed with other sun protection measures (see Directions), decreases the risk of skin cancer and early skin aging caused by the sun

■ When using this product, keep out of eyes. Rinse with water to remove

Active Ingredient

Avobenzone 2.80%
Homosalate 7.30%
Octisalate 4.80%
Octocrylene 9.50%

OTC-Do not use

Do not use ■ on damaged skin, ■ on broken skin

Keep out of reach of children. If product is swallowed, get medical help or contact a Poison Control Center right away

Directions

■ Apply liberally 15 minutes before sun exposure. Reapply at least every two hours
■ Sun protection measures. Spending time in the sun increases your risk of skin cancer and early skin aging. To decrease this risk, regularly use a sunscreen with a broad spectrum SPF of 15 of higher and other sun protection measures including: 1) Limited time in the sun, especially from 10 am to 2 pm. 2) Wear long-sleeve shirts, pants, hats, and sunglasses
■ Ask a doctor to use for children under 6 months

Purpose

Purpose-Sunscreen

Other Information

Other Information ■ Protect the product in this container from excessive heat and direct sun

Inactive ingredients

Isododecane, Water (Aqua), Dimethicone, Butylene Glycol, PEG-10 Dimethicone, Dimethicone/Bis-Isobutyl PPG-20 Crosspolymer, Vinyl Dimethicone/Methicone Silsesquioxane Crosspolymer, Butyloctyl Salicylate, Cetyl PEG/PPG-10/1 Dimethicone, Pentylene Glycol, Disteardimonium Hectorite, Magnesium Sulfate, Lauryl PEG-8 Dimethicone, Synthetic Fluorphlogopite, Benzyl Glycol, Pyrus Communis (Pear) Fruit Extract, Potassium Cetyl Phosphate, Rosa Damascena Flower Water, Iris Florentina Root Extract, Silica, Ganoderma Lucidum (Mushroom) Stem Extract, Cucumis Melo (Melon) Fruit Extract, Ethylhexylglycerin, Aluminum Hydroxide, Isopropyl Titanium Triisostearate, Hedera Helix (Ivy) Leaf/Stem Extract, Boron Nitride, 1,2-Hexanediol, Hydroxyapatite, Quartz, Hydroxypropyltrimonium Hyaluronate, Myristic Acid, Cetearyl Alcohol, Sodium Hyaluronate, Oenothera Biennis (Evening Primrose) Flower, Pueraria Lobata Root Extract, Pinus Palustris Leaf Extract, Ulmus Davidiana Root Extract, Salix Alba (Willow) Bark Extract, Tocopherol, Hydrolyzed Hyaluronic Acid, Ascorbyl Propyl Hyaluronate, Sodium Acetylated Hyaluronate, Titanium Dioxide (CI 77891), Iron Oxides (CI 77492), Iron Oxides (CI 77491), Iron Oxides (CI 77499)

Questions or comments? 424-538-1951

Stop use and ask a doctor if rash occurs.

Warning

For external use only. When using this product, avoid contact with eyes. Stop use and ask a doctor if irritation occurs. Keep out of reach of children.

Indications and usage

Helps prevent sunburn, if used as directed with other sun protection measures (see Directions), decreases the risk of skin cancer and early skin aging caused by the sun

Package label Principal Display